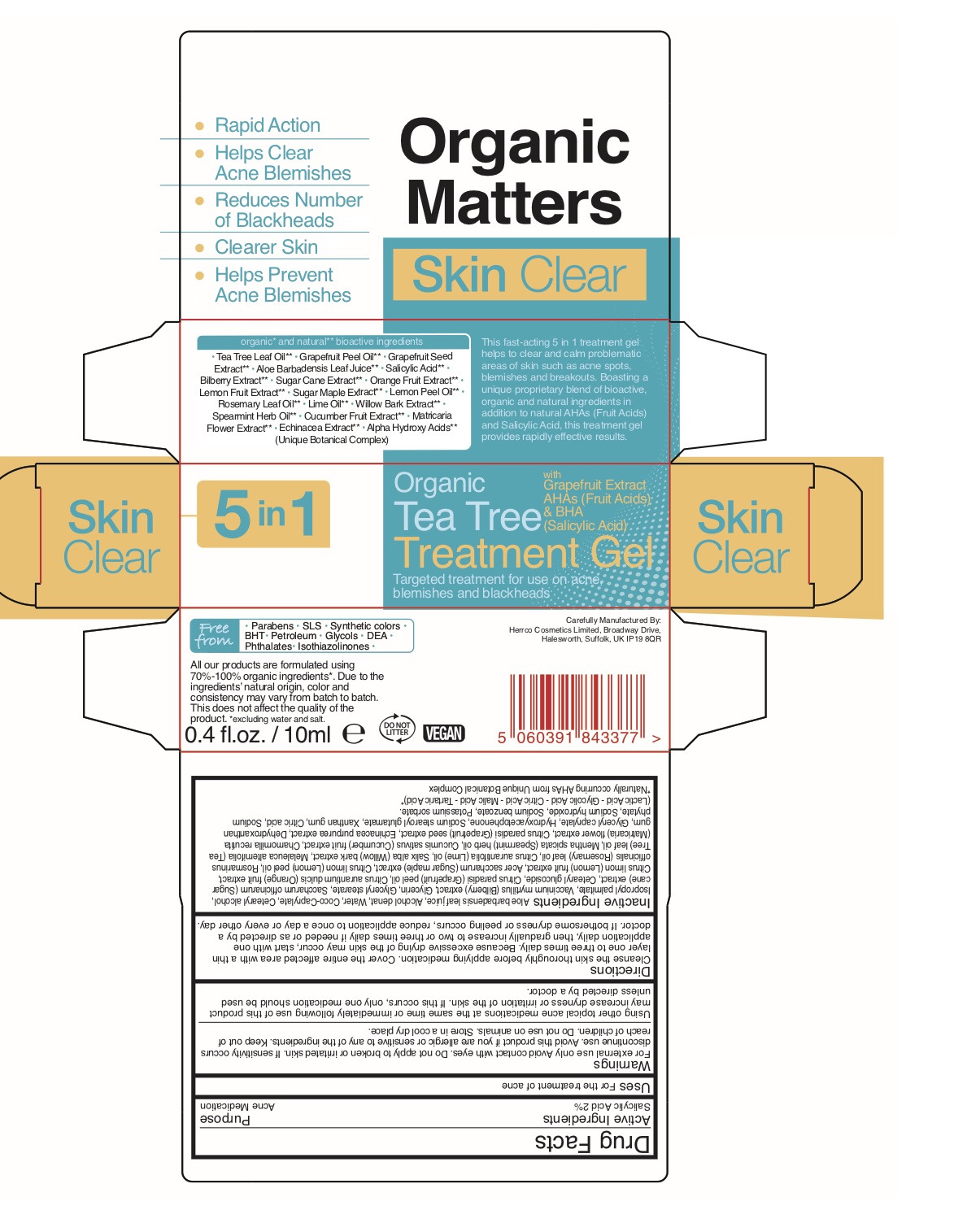 DRUG LABEL: Organic Tea Tree Treatment Gel
NDC: 71643-1019 | Form: GEL
Manufacturer: HERRCO COSMETICS LIMITED
Category: otc | Type: HUMAN OTC DRUG LABEL
Date: 20241220

ACTIVE INGREDIENTS: SALICYLIC ACID 2 g/100 mL
INACTIVE INGREDIENTS: BILBERRY; ALOE VERA LEAF; WATER; COCO-CAPRYLATE; ISOPROPYL PALMITATE; GLYCERIN; GLYCERYL MONOSTEARATE; SUGARCANE; ORANGE; ACER SACCHARUM BARK/SAP; LEMON OIL; ROSEMARY OIL; LIME OIL; SALIX ALBA BARK; TEA TREE OIL; SPEARMINT OIL; CUCUMBER; CHAMOMILE; CITRUS PARADISI SEED; ECHINACEA PURPUREA; DEHYDROXANTHAN GUM; GLYCERYL CAPRYLATE; SODIUM STEAROYL GLUTAMATE; XANTHAN GUM; CITRIC ACID MONOHYDRATE; PHYTATE SODIUM; SODIUM HYDROXIDE; POTASSIUM SORBATE; SODIUM BENZOATE; CETOSTEARYL ALCOHOL; CETEARYL GLUCOSIDE; GRAPEFRUIT PEEL; LEMON; ALCOHOL

Organic Tea Tree Treatment Gel

ACTIVE INGREDIENT

Salicylic Acid 2%

INDICATIONS AND USAGE

For the treatment of acne

Keep out of reach of children.

PURPOSE

Acne Treatment